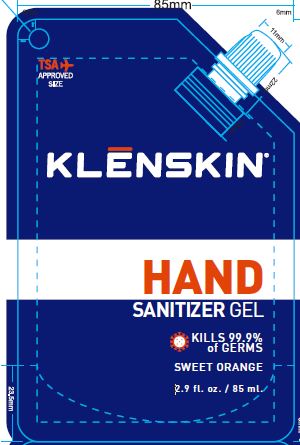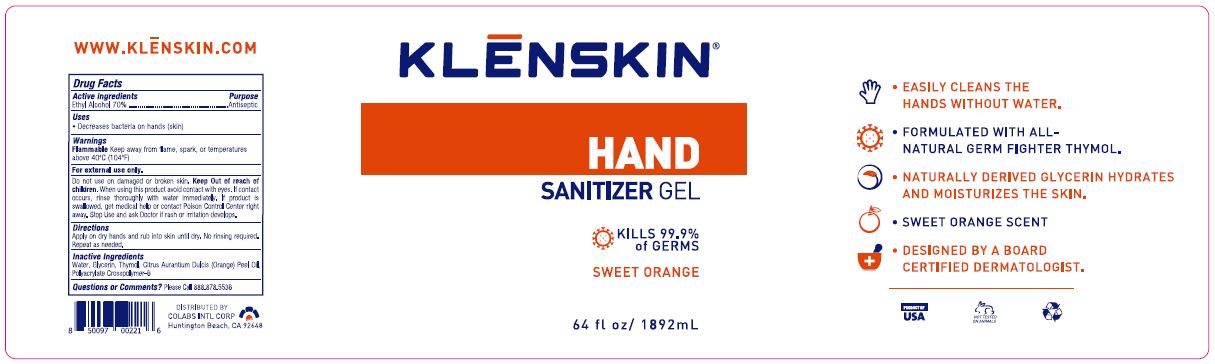 DRUG LABEL: KLENSKIN HAND SANITIZER
NDC: 61369-402 | Form: GEL
Manufacturer: CoLabs Intl. Corp
Category: otc | Type: HUMAN OTC DRUG LABEL
Date: 20220216

ACTIVE INGREDIENTS: ALCOHOL 70 mL/100 mL
INACTIVE INGREDIENTS: WATER; GLYCERIN; THYMOL; ORANGE OIL; AMMONIUM ACRYLOYLDIMETHYLTAURATE, DIMETHYLACRYLAMIDE, LAURYL METHACRYLATE AND LAURETH-4 METHACRYLATE COPOLYMER, TRIMETHYLOLPROPANE TRIACRYLATE CROSSLINKED (45000 MPA.S)

COLABS - KLENSKIN HAND SANITIZER GEL (70% ETHYL ALCOHOL), 61369-402

ACTIVE INGREDIENTS

ETHYL ALCOHOL 70% W/W

PURPOSE

ANTISEPTIC

USES

- Decreases bacteria on hands (skin)
- Recommended for repeated use

WARNINGS

Flammable Keep away from flame, spark, or temperatures above 40°C (104°F)

For external use only.

Do not use on damaged or broken skin.

KEEP OUT OF REACH OF CHILDREN.

When using this product avoid contact with eyes. If contact occurs, rinse thoroughly with water immediately. If product is
swallowed, get medical help or contact Poison Control Center right away. Stop Use and ask Doctor if rash or irritation develops.

DIRECTIONS

Apply on dry hand and rub into skin until dry. No rinsing required. Repeat as needed.

INACTIVE INGREDIENTS

Water, Glycerin, Thymol, Citrus Aurantium Dulcis (Orange) Peel Oil, Polyacrylate Crosspolymer-6

QUESTIONS OR COMMENTS?

PLEASE CALL TOLL FREE 888.878.5536